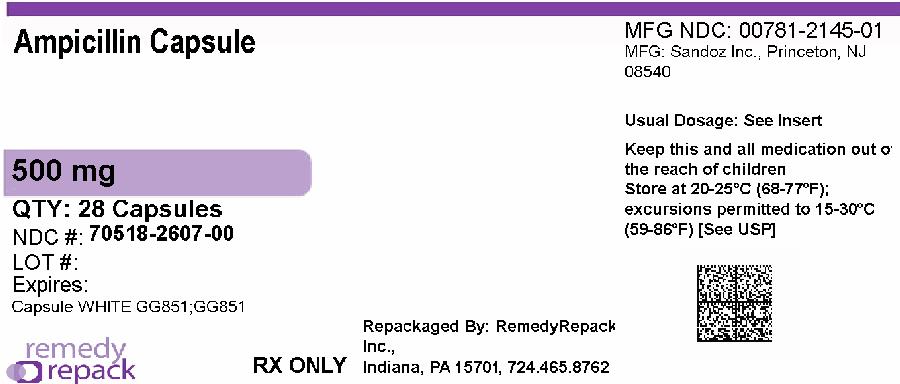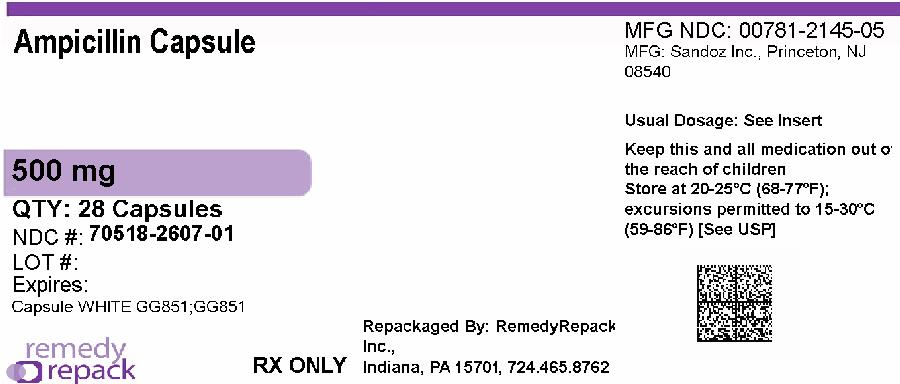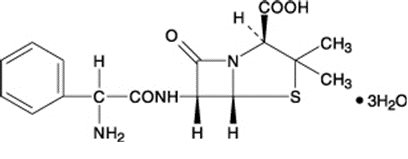 DRUG LABEL: Ampicillin
NDC: 70518-2607 | Form: CAPSULE
Manufacturer: REMEDYREPACK INC.
Category: prescription | Type: HUMAN PRESCRIPTION DRUG LABEL
Date: 20260210

ACTIVE INGREDIENTS: AMPICILLIN TRIHYDRATE 500 mg/1 1
INACTIVE INGREDIENTS: AMMONIA; FERROSOFERRIC OXIDE; GELATIN, UNSPECIFIED; MAGNESIUM STEARATE; POTASSIUM HYDROXIDE; PROPYLENE GLYCOL; SHELLAC; TITANIUM DIOXIDE

Ampicillin Capsules, USP

Rx Only

To reduce the development of drug-resistant bacteria and maintain the effectiveness of ampicillin and other antibacterial drugs, ampicillin should be used only to treat or prevent infections that are proven or strongly suspected to be caused by bacteria.

DESCRIPTION

Ampicillin trihydrate is a semisynthetic penicillin derived from the basic penicillin nucleus, 6- aminopenicillanic acid. Ampicillin is designated chemically as (2S, 5 R, 6 R)-6-[(R)-2-Amino-2-phenylacetamido]-3,3- dimethyl-7-oxo-4-thia-1-azabicyclo [3.2.0] heptane-2- carboxylic acid. Its structural formula is:

Molecular formula: C16H19N3O4S ·3 H2O

Molecular weight: 403.5

Ampicillin capsules, USP for oral administration provide ampicillin trihydrate equivalent to 250 mg and 500 mg ampicillin. Inactive ingredients: black iron oxide, gelatin, magnesium stearate, titanium dioxide, shellac, propylene glycol, ammonium hydroxide, and potassium hydroxide.

CLINICAL PHARMACOLOGY

Ampicillin is bactericidal at low concentrations and is clinically effective not only against the gram-positive organisms usually susceptible to penicillin G but also against a variety of gram-negative organisms. It is stable in the presence of gastric acid and is well absorbed from the gastrointestinal tract. It diffuses readily into most body tissues and fluids; however, penetration into the cerebrospinal fluid and brain occurs only with meningeal inflammation. Ampicillin is excreted largely unchanged in the urine; its excretion can be delayed by concurrent administration of probenecid which inhibits the renal tubular secretion of ampicillin. In blood serum, ampicillin is the least bound of all the penicillins; an average of about 20 percent of the drug is bound to plasma proteins as compared to 60 to 90 percent of the other penicillins. The administration of 500 mg dose of ampicillin capsules results in an average peak blood serum level of approximately 3.0 mcg/mL.

Microbiology

Mechanism of Action

Ampicillin is similar to penicillin in its bactericidal action against susceptible bacteria during the stage of active multiplication. It acts through the inhibition of cell wall biosynthesis that leads to the death of the bacteria.

Mechanism of Resistance

Resistance to ampicillin is mediated primarily through enzymes called beta-lactamases that cleave the beta-lactam ring of ampicillin, rendering it inactive.

Antimicrobial Activity

Ampicillin has been shown to be active against most isolates of the following bacteria, both in vitroand in clinical infections, as described in the INDICATIONS AND USAGEsection.

Gram-positive Bacteria

Enterococcusspp.

Staphylococcusspp. (non-penicillinase-producing)

Streptococcus pneumoniae

Streptococcus pyogenes

Viridans group streptococci

Gram-negative Bacteria

Escherichia coli

Haemophilus influenzae(non-penicillinase-producing)

Neisseria gonorrhoeae

Neisseria meningitidis

Proteus mirabilis

Salmonellaspp.

Shigellaspp.

The following in vitrodata are available, but their clinical significance is unknown. At least 90 percent of the following bacteria exhibit an in vitrominimum inhibitory concentration (MIC) less than or equal to 0.12 mcg/mL for ampicillin. However the efficacy of ampicillin in treating clinical infections due to these bacteria has not been established in adequate and well-controlled trials.

Gram-positive Bacteria

Bacillus anthracis

Corynebacterium xerosis

Anaerobic Bacteria

Clostridium spp.

Susceptibility Testing

For specific information regarding susceptibility test interpretive criteria and associated test methods and quality control standards recognized by FDA for this drug, please see: https://www.fda.gov/STIC.

INDICATIONS AND USAGE

To reduce the development of drug-resistant bacteria and maintain the effectiveness of ampicillin capsules, ampicillin for oral suspension and other antibacterial drugs, ampicillin capsules and ampicillin for oral suspension should be used only to treat or prevent infections that are proven or strongly suspected to be caused by bacteria. When culture and susceptibility information are available, they should be considered in selecting of modifying antimicrobial therapy, in the absence of such data, local epidemiology and susceptibility patterns contribute to the empiric selection of therapy.

Ampicillin capsules and ampicillin for oral suspension are indicated in the treatment of infections caused by susceptible strains of the designated organisms listed below:

Infections of the genitourinary tract including gonorrhea: E. coli, P. mirabilis, enterococci, Shigella, S. typhosaand other Salmonella, and nonpenicillinase producing N. gonorrhoeae.

Infections of the respiratory tract:Nonpenicillinase- producing H. influenzaeand staphylococci,and streptococciincluding streptococcus pneumoniae.

Infections of the gastrointestinal tract: Shigella, S. typhosaand other Salmonella, E. coli, P. mirabilis,and enterococci.

Meningitis: N. Meningitides.

Bacteriology studies to determine the causative organisms and their susceptibility to ampicillin should be performed. Therapy may be instituted prior to the results of susceptibility testing.

CONTRAINDICATIONS

The use of Ampicillin is contraindicated in individuals with a history of serious hypersensitivity reactions (e.g., anaphylaxis or Stevens-Johnson syndrome) to ampicillin or to other beta-lactam antibacterial drugs. Ampicillin is also contraindicated in infections caused by penicillinase-producing organisms.

Ampicillin is contraindicated in patients with a previous history of cholestatic jaundice/hepatic dysfunction associated with treatment with ampicillin.

WARNINGS

SERIOUS AND OCCASIONALLY FATAL HYPERSENSITIVITY (ANAPHYLACTIC) REACTIONS HAVE BEEN REPORTED IN PATIENTS ON PENICILLIN THERAPY. ALTHOUGH ANAPHYLAXIS IS MORE FREQUENT FOLLOWING PARENTERAL THERAPY, IT HAS OCCURRED IN PATIENTS ON ORAL PENICILLINS. THESE REACTIONS ARE MORE LIKELY TO OCCUR IN INDIVIDUALS WITH A HISTORY OF SENSITIVITY TO MULTIPLE ALLERGENS.

THERE HAVE BEEN REPORTS OF INDIVIDUALS WITH A HISTORY OF PENICILLIN HYPERSENSITIVITY WHO HAVE EXPERIENCED SEVERE REACTIONS WHEN TREATED WITH CEPHALOSPORINS. BEFORE THERAPY WITH ANY PENICILLIN, CAREFUL INQUIRY SHOULD BE MADE CONCERNING PREVIOUS HYPERSENSITIVITY REACTIONS TO PENICILLINS, CEPHALOSPORINS OR OTHER ALLERGENS. IF AN ALLERGIC REACTION OCCURS, APPROPRIATE THERAPY SHOULD BE CONSIDERED.

SERIOUS ANAPHYLACTIC REACTIONS REQUIRE IMMEDIATE EMERGENCY TREATMENT WITH EPINEPHRINE. OXYGEN, INTRAVENOUS STEROIDS, AND AIRWAY MANAGEMENT, INCLUDING INTUBATION, SHOULD ALSO BE ADMINISTERED AS INDICATED.

Severe Cutaneous Adverse Reactions

Ampicillin may cause severe cutaneous adverse reactions (SCARs), such as toxic epidermal necrolysis

(TEN), Stevens-Johnson syndrome (SJS), drug reaction with eosinophilia and systemic symptoms

(DRESS), exfoliative dermatitis, erythema multiforme, and acute generalized exanthematous pustulosis

(AGEP). If patients develop a skin rash, they should be monitored closely, and ampicillin discontinued if

lesions progress.

Hepatotoxicity

Hepatic dysfunction, including hepatitis and cholestatic jaundice has been associated with the use of

ampicillin. Hepatic toxicity is usually reversible; however, deaths have been reported. Hepatic function

should be monitored at regular intervals in patients with hepatic impairment.

Clostridioides difficile-Associated Diarrhea

Clostridioides difficile-associated diarrhea (CDAD) has been reported with use of nearly all antibacterial

agents, including ampicillin, and may range in severity from mild diarrhea to fatal colitis. Treatment with

antibacterial agents alters the normal flora of the colon leading to overgrowth of C. difficile.

C. difficileproduces toxins A and B which contribute to the development of CDAD. Hypertoxin

producing strains of C. difficilecause increased morbidity and mortality, as these infections can be

refractory to antimicrobial therapy and may require colectomy. CDAD must be considered in all patients

who present with diarrhea following antibacterial drug use. Careful medical history is necessary since

CDAD has been reported to occur over two months after the administration of antibacterial agents.

If CDAD is suspected or confirmed, ongoing antibacterial drug use not directed against C. difficilemay

need to be discontinued. Appropriate fluid and electrolyte management, protein supplementation,

antibacterial treatment of C. difficile, and surgical evaluation should be instituted as clinically indicated.

PRECAUTIONS

General

A high percentage of patients with mononucleosis who receive ampicillin develop a skin rash. Thus,

ampicillin class antibacterial should not be administered to patients with mononucleosis. In patients

treated with ampicillin the possibility of superinfections with mycotic or bacterial pathogens should be

kept in mind during therapy. If superinfections occur (usually involving Pseudomonas or Candida), the

drug should be discontinued and/or appropriate therapy instituted.

Prescribing ampicillin in the absence of a proven or strongly suspected bacterial infection or a prophylactic indication is unlikely to provide benefit to the patient and increases the risk of the development of drug-resistant bacteria.

Prolonged use of antibiotics may promote the overgrowth of nonsusceptible organisms, including fungi. Should superinfection occur, appropriate measures should be taken.

Patients with gonorrhea who also have syphilis should be given additional appropriate parenteral penicillin treatment.

Treatment with ampicillin does not preclude the need for surgical procedures, particularly in staphylococcal infections.

Information for the Patient

1. The patient should inform the physician of any history of sensitivity to allergens, including previous hypersensitivity reactions to penicillins and cephalosporins (see WARNINGS).
2. Advise patients about the signs and symptoms of serious skin manifestations. Instruct patients to stop
3. taking ampicillin immediately and promptly report the first signs or symptoms of skin rash, mucosal
4. lesions, or any other sign of hypersensitivity [see WARNINGS].
5. Diarrhea is a common problem caused by antibacterials which usually ends when the antibacterial is
6. discontinued. Sometimes after starting treatment with antibacterials, patients can develop watery and
7. bloody stools (with or without stomach cramps and fever) even as late as two or more months after
8. having taken the last dose of the antibacterial. If this occurs, patients should contact their physician
9. as soon as possible.
10. Ampicillin should be taken with a full glass (8 oz) of water, one-half hour before or two hours after meals.
11. Diabetic patients should consult with the physician before changing diet or dosage of diabetes medication (see PRECAUTIONS–Drug/Laboratory Test Interactions).
12. Patients should be counseled that antibacterial drugs including ampicillin should only be used to treat bacterial infections. They do not treat viral infections (e.g., the common cold). When ampicillin is prescribed to treat a bacterial infection, patients should be told that although it is common to feel better early in the course of therapy, the medication should be taken exactly as directed. Skipping doses or not completing the full course of therapy may: (1) decrease the effectiveness of the immediate treatment, and (2) increase the likelihood that bacteria will develop resistance and will not be treatable by ampicillin or other antibacterial drugs in the future.

Repackaged By / Distributed By: RemedyRepack Inc.

625 Kolter Drive, Indiana, PA 15701

(724) 465-8762

Laboratory Tests

In prolonged therapy, and particularly with high dosage regimens, periodic evaluation of the renal, hepatic, and hematopoietic systems is recommended.

In streptococcal infections, therapy, must be sufficient to eliminate the organism (10 days minimum); otherwise the sequelae of streptococcal disease may occur. Cultures should be taken following completion of treatment to determine whether streptococci have been eradicated.

Cases of gonococcal infection with a suspected lesion of syphilis should have darkfield examinations ruling out syphilis before receiving ampicillin. Patients who do not have suspected lesions of syphilis and are treated with ampicillin should have a follow-up serologic test for syphilis each month for four months to detect syphilis that may have been masked from treatment for gonorrhea.

Drug Interactions

When administered concurrently, the following drugs may interact with ampicillin.

Allopurinol: Substantially increased incidence of skin rashes in patients receiving both drugs as compared

to patients receiving ampicillin alone. It is not known whether this potentiation of ampicillin rashes is due

to allopurinol or the hyperuricemia present in these patients.

Bacteriostatic Antibiotics: Chloramphenicol, erythromycins, sulfonamides, or tetracyclines may interfere with the bactericidal effect of penicillins. This has been demonstrated in vitro;however, the clinical significance of this interaction is not well-documented.

Oral Contraceptives: May be less effective and increased breakthrough bleeding may occur.

Probenecid: May decrease renal tubular secretion of ampicillin resulting in increased blood levels and/or ampicillin toxicity.

Drug/Laboratory Test Interactions

After treatment with ampicillin, a false-positive reaction for glucose in the urine may occur with copper sulfate tests (Benedict’s solution, Fehling’s solution, or Clinitest®tablets) but not with enzyme based tests such as Clinistix®and Tes-Tape®. Following administration of ampicillin to pregnant women, a transient

decrease in plasma concentration of total conjugated estriol, estriol-glucuronide, conjugated estrone and

estradiol has been noted.

Carcinogenesis, Mutagenesis, Impairment of Fertility

Long-term studies in animals have not been performed to evaluate carcinogenesis, mutagenesis, or impairment of fertility in males or females.

Pregnancy

Teratogenic Effects

Reproduction studies in animals have revealed no evidence of impaired fertility or harm to the fetus due to penicillin. There are, however, no adequate and well-controlled studies in pregnant women. Because animal reproduction studies are not always predictive of human response, penicillin should be used during pregnancy only if clearly needed. (See PRECAUTIONS-Drug/Laboratory Test Interactions.)

Labor and Delivery

Oral ampicillin-class antibiotics are poorly absorbed during labor. Studies in guinea pigs showed that intravenous administration of ampicillin slightly decreased the uterine tone and frequency of contractions, but moderately increased the height and duration of contractions. However, it is not known whether use of these drugs in humans during labor or delivery has immediate or delayed adverse effects on the fetus, prolongs the duration of labor, or increases the likelihood that forceps delivery or other obstetrical intervention or resuscitation of the newborn will be necessary.

Nursing Mothers

Ampicillin-class antibiotics are excreted in milk. Ampicillin used by nursing mothers may lead to sensitization of infants; therefore, caution should be exercised when ampicillin is administered to a nursing woman.

Pediatric Use

Penicillins are excreted primarily unchanged by the kidney; therefore, the incompletely developed renal function in neonates and young infants will delay the excretion of penicillin. Administration to neonates and young infants should be limited to the lowest dosage compatible with an effective therapeutic regimen (see DOSAGE AND ADMINISTRATION).

ADVERSE REACTIONS

As with other penicillins, it may be expected that untoward reactions will be essentially limited to sensitivity phenomena. They are more likely to occur in individuals who have previously demonstrated hypersensitivity to penicillin and in those with a history of allergy, asthma, hay fever, or urticaria.

The following adverse reactions have been reported as associated with the use of ampicillin:

Infections and Infestations: Clostridioides difficile-associated diarrhea (see WARNINGSsection).

Gastrointestinal: glossitis, stomatitis, nausea, vomiting, enterocolitis, pseudomembranous colitis, and diarrhea. These reactions are usually associated with oral dosage forms of the drugs.

Hypersensitivity Reactions: Severe cutaneous adverse reactions, including Stevens-Johnson syndrome

(SJS), toxic epidermal necrolysis (TEN), drug reaction with eosinophilia and systemic symptoms

(DRESS), angioedema, and acute generalized exanthematous pustulosis (AGEP) have been reported in

beta-lactam antibiotics (see WARNINGS). An erythematous, mildly pruritic, maculopapular skin rash has been reported fairly frequently. The rash, which usually does not develop within the first week of therapy, may cover the entire body including the soles, palms, and oral mucosa. The eruption usually disappears in three to seven days. Other hypersensitivity reactions that have been reported are: skin rash, pruritus, urticaria, erythema multiforme, and an occasional case of exfoliative dermatitis. Linear IgA bullous dermatosis has been reported. Anaphylaxis is the most serious reaction experienced and has usually been associated with the parenteral dosage form of the drug.

NOTE: Urticaria, other skin rashes, and serum sickness-like reactions may be controlled by antihistamines, and, if necessary, systemic corticosteroids. Whenever such reactions occur, ampicillin should be discontinued unless, in the opinion of the physician, the condition being treated is life-threatening, and amenable only to ampicillin therapy. Serious anaphylactic reactions require emergency measures (see WARNINGS).

Liver: Moderate elevation in serum glutamic oxaloacetic transaminase (SGOT) has been noted, but the significance of this finding is unknown.

Hemic and Lymphatic Systems: Anemia, thrombocytopenia, thrombocytopenic purpura, eosinophilia, leukopenia, and agranulocytosis have been reported during therapy with penicillins. These reactions are usually reversible on discontinuation of therapy and are believed to be hypersensitivity phenomena.

Other adverse reactions that have been reported with the use of ampicillin are laryngeal stridor and high fever. An occasional patient may complain of sore mouth or tongue as with any oral penicillin preparation.

OVERDOSAGE

In case of overdosage, discontinue medication, treat symptomatically and institute supportive measures as required. In patients with renal function impairment, ampicillin-class antibiotics can be removed by hemodialysis but not by peritoneal dialysis.

DOSAGE AND ADMINISTRATION

Adults and children weighing over 20 kg:

For genitourinary or gastrointestinal tract infections other than gonorrhea in men and women,the usual dose is 500 mg qid in equally spaced doses; severe or chronic infections may require larger doses. For the treatment of gonorrhea in both men and women, a single oral dose of 3.5 grams of ampicillin administered simultaneously with 1 gram of probenecid is recommended. Physicians are cautioned to use no less than the above recommended dosage for the treatment of gonorrhea. Follow-up cultures should be obtained from the original site(s) of infection 7 to 14 days after therapy. In women, it is also desirable to obtain culture test-of-cure from both the endocervical and anal canals. Prolonged intensive therapy is needed for complications such as prostatitis and epididymitis.

For respiratory tract infections, the usual dose is 250 mg qid in equally spaced doses.

Pediatric patients weighing 20 kg or less:

For genitourinary or gastrointestinal tract infections, the usual dose is 100 mg/kg/day total, qid in equally divided and spaced doses. For respiratory tract infections,the usual dose is 50 mg/kg/day total, in equally divided and spaced doses three to four times daily. Doses for children should not exceed doses recommended for adults.

All Patients, Irrespective of Age and Weight:

Larger doses may be required for severe or chronic infections. Although ampicillin is resistant to degradation by gastric acid, it should be administered at least one-half hour before or two hours after meals for maximal absorption. Except for the single dose regimen for gonorrhea referred to above, therapy should be continued for a minimum of 48 to 72 hours after the patient becomes asymptomatic or evidence of bacterial eradication has been obtained. In infections caused by hemolytic strains of streptococci, a minimum of 10 days’ treatment is recommended to guard against the risk of rheumatic fever or glomerulonephritis (see PRECAUTIONS–Laboratory Tests). In the treatment of chronic urinary or gastrointestinal infections, frequent bacteriologic and clinical appraisal is necessary during therapy and may be necessary for several months afterwards. Stubborn infections may require treatment for several weeks. Smaller doses than those indicated above should not be used.

HOW SUPPLIED

Ampicillin capsules, USP: Each capsule, for oral administration, contains ampicillin trihydrate equivalent to 500 mg ampicillin, and are supplied as:

500 mg: White, opaque, hard gelatin capsules, imprinted in black ink GG 851/GG 851.

NDC: 70518-2607-00

NDC: 70518-2607-01

PACKAGING: 28 in 1 BOTTLE PLASTIC

PACKAGING: 28 in 1 BOTTLE PLASTIC

Store at 20°C to 25°C (68°F to 77°F) [see USP Controlled Room Temperature].

Dispense in a tight container.

Repackaged and Distributed By:

Remedy Repack, Inc.

625 Kolter Dr. Suite #4 Indiana, PA 1-724-465-8762

PACKAGE LABEL

DRUG: Ampicillin

GENERIC: Ampicillin

DOSAGE: CAPSULE

ADMINSTRATION: ORAL

NDC: 70518-2607-0

NDC: 70518-2607-1

COLOR: white

SHAPE: CAPSULE

SCORE: No score

SIZE: 22 mm

IMPRINT: GG851;GG851

PACKAGING: 28 in 1 BOTTLE, PLASTIC

PACKAGING: 28 in 1 BOTTLE, PLASTIC

ACTIVE INGREDIENT(S):

- AMPICILLIN TRIHYDRATE 500mg in 1

INACTIVE INGREDIENT(S):

- AMMONIA
- FERROSOFERRIC OXIDE
- GELATIN, UNSPECIFIED
- MAGNESIUM STEARATE
- POTASSIUM HYDROXIDE
- PROPYLENE GLYCOL
- SHELLAC
- TITANIUM DIOXIDE